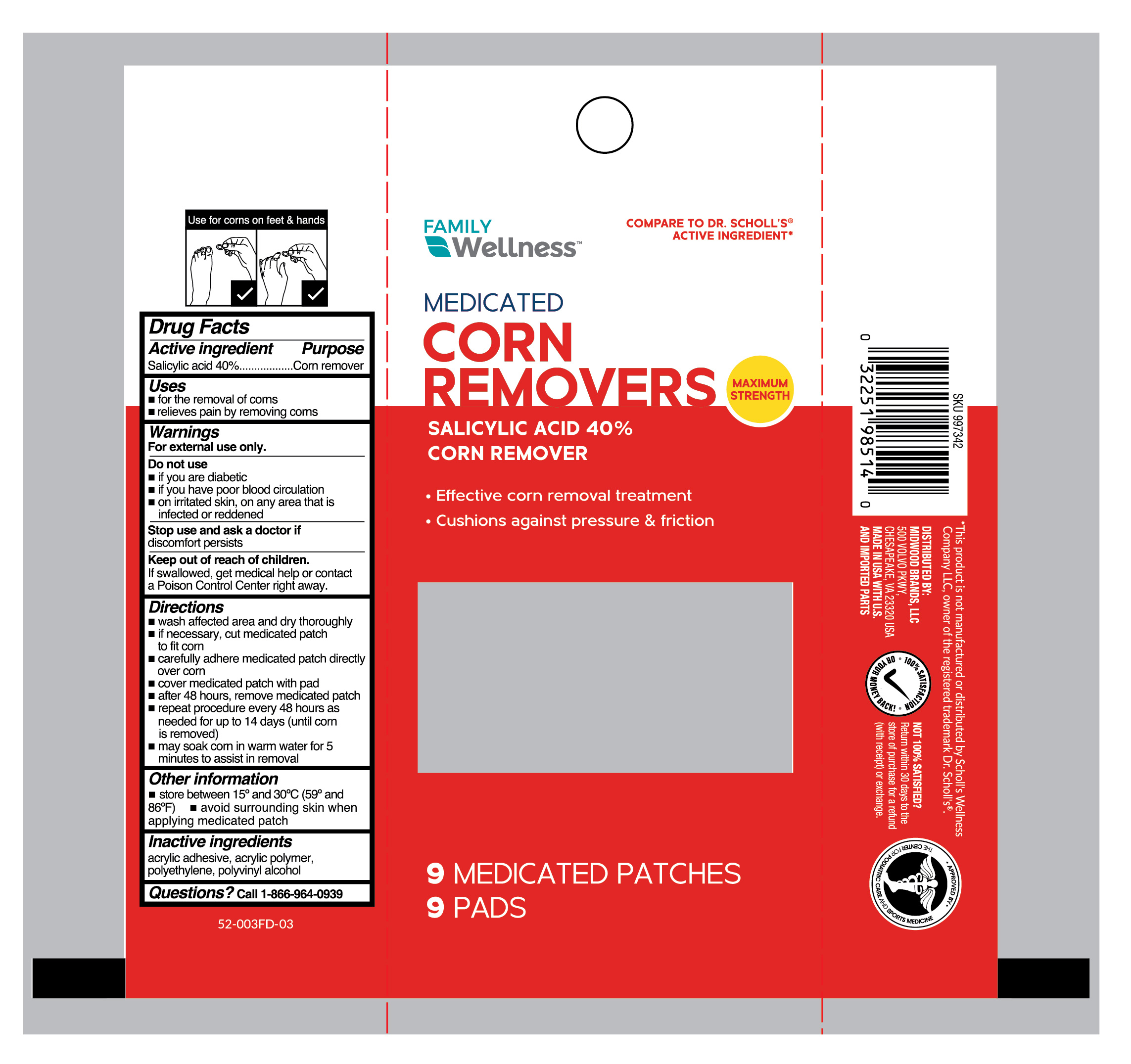 DRUG LABEL: Medicated Corn Removers
NDC: 55319-476 | Form: PATCH
Manufacturer: Family Dollar Services, Inc
Category: otc | Type: HUMAN OTC DRUG LABEL
Date: 20251230

ACTIVE INGREDIENTS: SALICYLIC ACID 400 mg/1 g
INACTIVE INGREDIENTS: HIGH DENSITY POLYETHYLENE; POLYVINYL ALCOHOL, UNSPECIFIED

Family Wellness Medicated Corn Removers

Active ingredient

Salicylic acid 40%

Purpose

Corn remover

Use

- for the removal of corns
- relieves pain by removing corns

Warnings

For external use only.

Do not use

- if you are a diabetic
- if you have poor blood circulation
- on irritated skin, on any area that is infected or reddened

Stop use and ask a doctor

if discomfort persists

Keep out of reach of children.

If swallowed, get medical help or contact a Poison Control Center right away.

Directions

- wash affected area and dry area thoroughly
- if necessary, cut medicated patch to fit corn
- carefully adhere medicated patch directly over corn
- cover medicated patch with pad
- after 48 hours, remove medicated patch
- repeat procedure every 48 hours as needed for up to 14 days (until corn is removed)
- may soak corn in warm water for 5 minutes to assist in removal

Other information

store between 15° and 30°C (59° and 86°F)

avoid surrounding skin when applying medicated patch

Inactive ingredients

acrylic adhesive, acrylic polymer, polyethylene, polyvinyl alcohol

Questions?

call 1-866-964-0939

Principal Display Panel

FAMILY

Wellness

MEDICATED

CORN

REMOVERS

SALICYLIC ACID 40%

CORN REMOVER

Effective corn removal treatment

Cushions against pressure & friction

9 Medicated Patches | 9 Pads